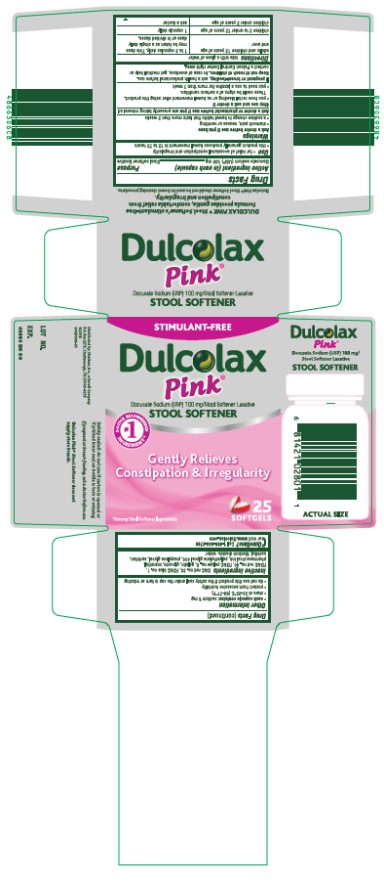 DRUG LABEL: Dulcolax Pink Stool Softener
NDC: 41167-0281 | Form: CAPSULE, LIQUID FILLED
Manufacturer: Chattem, Inc.
Category: otc | Type: HUMAN OTC DRUG LABEL
Date: 20260114

ACTIVE INGREDIENTS: DOCUSATE SODIUM 100 mg/1 1
INACTIVE INGREDIENTS: D&C RED NO. 33; FD&C BLUE NO. 1; FD&C RED NO. 40; FD&C YELLOW NO. 6; GELATIN; GLYCERIN; MANNITOL; POLYETHYLENE GLYCOL 400; PROPYLENE GLYCOL; SORBITAN; SORBITOL; TITANIUM DIOXIDE; WATER

Dulcolax Pink Stool Softener

Dulcolax Pink®

Stool Softener

Drug Facts

Active ingredient (in each capsule)

Docusate sodium (USP) 100 mg

Purpose

Stool softener laxative

Use

● for relief of occasional constipation and irregularity

● this product generally produces bowel movement in 12 to 72 hours

Warnings

Do not use

● if you are presently taking mineral oil, unless told to do so by a doctor

Ask a doctor before use if you have

● stomach pain, nausea or vomiting

● a sudden change in bowel habits that lasts more than 2 weeks

Stop use and ask a doctor if

● you have rectal bleeding or no bowel movement after using this product. These could be signs of a serious condition.

● you need to use a laxative for more than 1 week

If pregnant or breast-feeding,

ask a health professional before use.

Keep out of reach of children.

In case of overdose, get medical help or contact a Poison Control Center right away.

Directions

take with a glass of water

adults and children 12 years of age and over 1 to 3 capsules daily. This dose may be taken as a single daily dose or in divided doses.

children 2 to under 12 years of age 1 capsule daily

children under 2 years of age ask a doctor

Other information

● each capsule contains: sodium 6 mg

● store at 20°-25°C (68°-77°F)

● protect from excessive humidity

● do not use this product if the safety seal under the cap is torn or missing

Inactive ingredients

D&C red no. 33, FD&C blue no. 1, FD&C red no. 40, FD&C yellow no. 6, gelatin, glycerin, mannitol, pharmaceutical ink, polyethylene glycol 400, propylene glycol, sorbitan, sorbitol, titanium dioxide, water

Questions?

Call 1-866-844-2798 or visit www.Dulcolax.com

PRINCIPAL DISPLAY PANEL

Dulcolax
Pink
STOOL SOFTENER
25 SOFTGELS